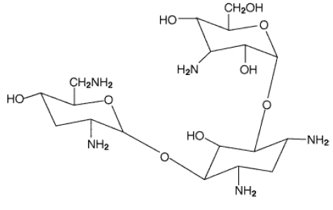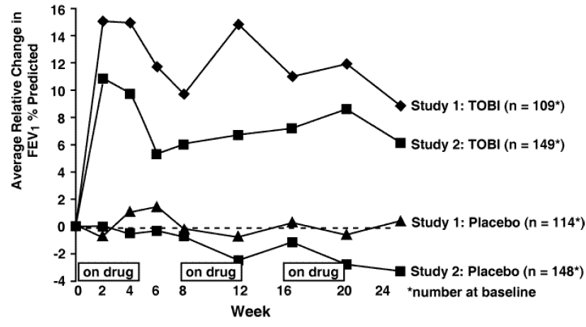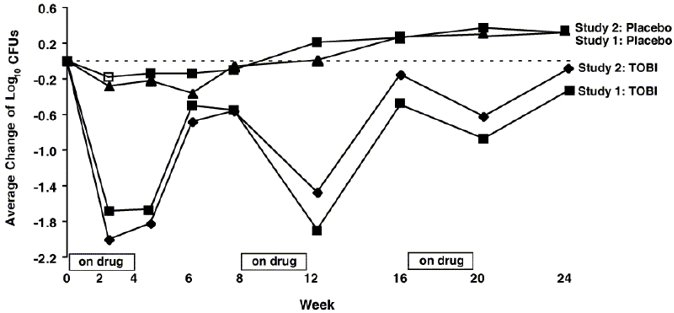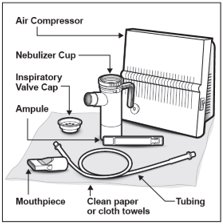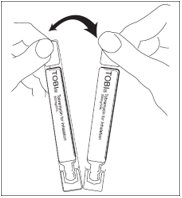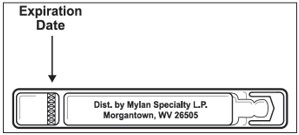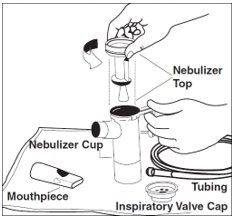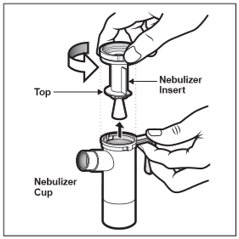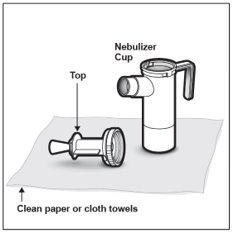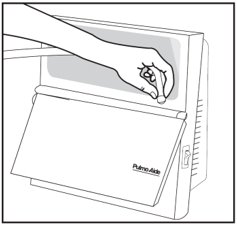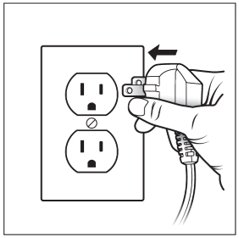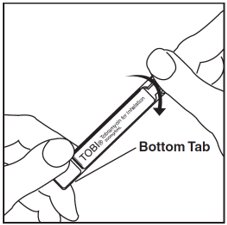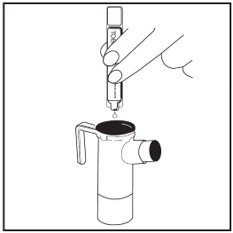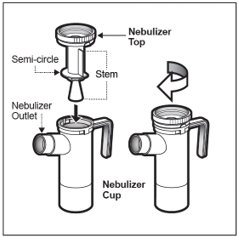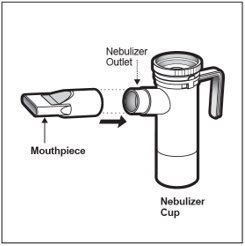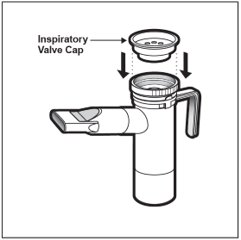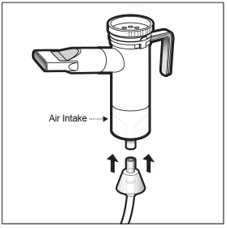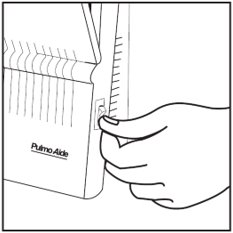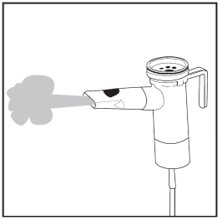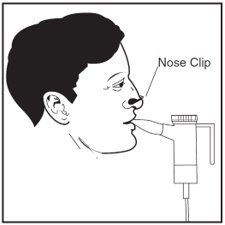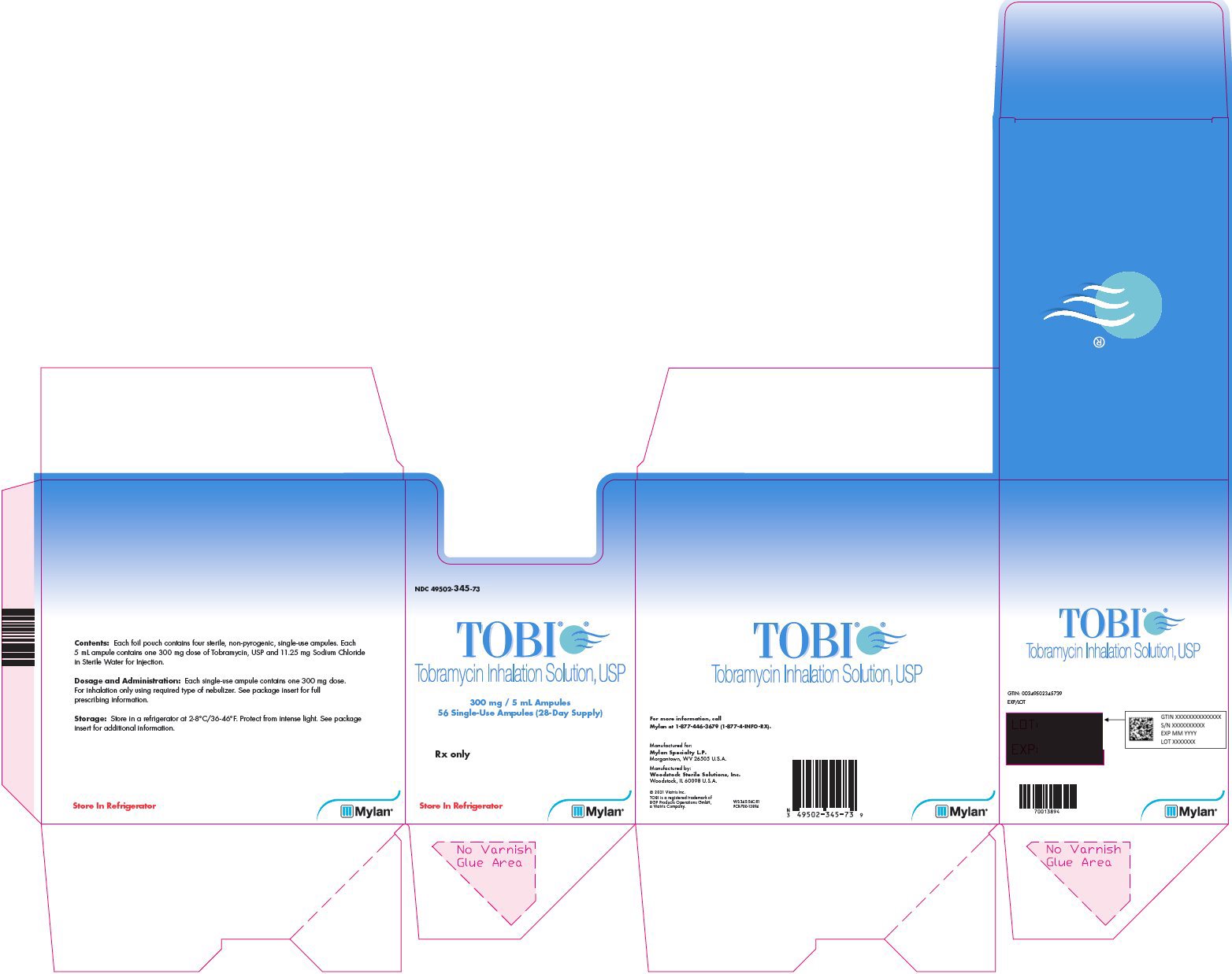 DRUG LABEL: TOBI
NDC: 49502-345 | Form: SOLUTION
Manufacturer: Viatris Specialty LLC
Category: prescription | Type: HUMAN PRESCRIPTION DRUG LABEL
Date: 20230215

ACTIVE INGREDIENTS: TOBRAMYCIN 300 mg/5 mL
INACTIVE INGREDIENTS: SODIUM CHLORIDE 11.25 mg/5 mL; SODIUM HYDROXIDE; WATER; SULFURIC ACID

HIGHLIGHTS OF PRESCRIBING INFORMATION

These highlights do not include all the information needed to use TOBI safely and effectively. See full prescribing information for TOBI.
TOBI® (tobramycin inhalation solution), for oral inhalation use
Initial U.S. Approval: 1975

RECENT MAJOR CHANGES

Warnings and Precautions, Ototoxicity (5.2) 2/2023

1 INDICATIONS AND USAGE

TOBI is an aminoglycoside antibacterial indicated for the management of cystic fibrosis in adults and pediatric patients 6 years of age and older with Pseudomonas aeruginosa. (1)

Safety and efficacy have not been demonstrated in patients under the age of 6 years, patients with forced expiratory volume in 1 second (FEV1) <25% or >75% predicted, or patients colonized with Burkholderia cepacia. (1)

2 DOSAGE AND ADMINISTRATION

- For oral inhalation only. (2.1)
- The recommended dosage for adults and pediatric patients 6 years of age and older is one single-dose ampoule (300 mg) twice daily by oral inhalation in alternating periods of 28 days on drug, followed by 28 days off drug. (2.1)
- Dosage is not adjusted by weight. (2.1)
- Take doses as close to 12 hours apart as possible; but not less than 6 hours apart. (2.1)
- Administer each 300 mg dose by inhalation using a hand-held PARI LC PLUS Reusable Nebulizer with a DeVilbiss Pulmo-Aide compressor. (2.2)

3 DOSAGE FORMS AND STRENGTHS

Inhalation Solution: 300 mg per 5 mL solution in a single-dose ampoule (3)

4 CONTRAINDICATIONS

Known hypersensitivity to any aminoglycoside (4)

5 WARNINGS AND PRECAUTIONS

- Bronchospasm: Can occur with inhalation of TOBI. Treat as medically appropriate, if it occurs. (5.1)
- Ototoxicity: Tinnitus and hearing loss have been reported in patients receiving TOBI. If noted, manage as medically appropriate, including potentially discontinuing TOBI. (5.2)
- Nephrotoxicity: Has been associated with aminoglycosides as a class. If nephrotoxicity develops, manage the patient as medically appropriate, including potentially discontinuing TOBI. (5.3)
- Neuromuscular Disorders: Aminoglycosides may aggravate muscle weakness because of a potential curare-like effect on neuromuscular function. If neuromuscular blockade occurs, it may be reversed by the administration of calcium salts but mechanical assistance may be necessary. (5.4)
- Embryo-fetal Toxicity: Aminoglycosides can cause fetal harm (5.5, 8.1)

6 ADVERSE REACTIONS

Most common adverse reactions (incidence >5%) are increased cough, pharyngitis, increased sputum, dyspnea, hemoptysis, decreased lung function, voice alteration, taste perversion and rash. (6.1)

To report SUSPECTED ADVERSE REACTIONS, contact Mylan at 1-877-446-3679 (1-877-4-INFO-RX) or FDA at 1-800-FDA-1088 or www.fda.gov/medwatch.

7 DRUG INTERACTIONS

- Concurrent and/or sequential use of TOBI with other drugs with neurotoxic, nephrotoxic, or ototoxic potential should be avoided. (7.1)
- Concomitant administration with ethacrynic acid, furosemide, urea, or intravenous mannitol is not recommended due to possible enhancement of aminoglycoside toxicity. (7.2)

FULL PRESCRIBING INFORMATION

1 INDICATIONS AND USAGE

TOBI is indicated for the management of cystic fibrosis in adults and pediatric patients 6 years of age and older with Pseudomonas aeruginosa.

Safety and efficacy have not been demonstrated in patients under the age of 6 years, patients with forced expiratory volume in 1 second (FEV1) <25% or >75% predicted, or patients colonized with Burkholderia cepacia [see Clinical Studies (14)].

2 DOSAGE AND ADMINISTRATION

2.1 Dosage

TOBI is for oral inhalation only [see Dosage and Administration (2.2)]. The recommended dosage of TOBI for both adults and pediatric patients 6 years of age and older is one single-dose ampoule (300 mg) administered twice daily for 28 days. Dosage is not adjusted by weight. All patients should be administered 300 mg twice daily.

TOBI is administered twice daily in alternating periods of 28 days. After 28 days of therapy, patients should stop TOBI therapy for the next 28 days, and then resume therapy for the next 28 day on/28 day off cycle. The doses should be taken as close to 12 hours apart as possible; they should not be taken less than 6 hours apart.

If patients miss a dose, they should take it as soon as possible anytime up to 6 hours prior to their next scheduled dose. If less than 6 hours remain before the next dose, wait until their next scheduled dose.

2.2 Administration Instructions

TOBI is administered by oral inhalation over an approximately 15-minute period, using a hand-held PARI LC PLUS Reusable Nebulizer with a DeVilbiss Pulmo-Aide compressor. TOBI should not be diluted or mixed with dornase alfa or other medications in the nebulizer. TOBI is not for subcutaneous, intravenous or intrathecal administration.

Prior to administration of TOBI, read the Patient Information/Instructions for Use for TOBI for detailed information on how to use TOBI, and follow the manufacturer’s instructions for use and care of the PARI LC PLUS Reusable Nebulizer and DeVilbiss Pulmo-Aide air compressor. TOBI is inhaled while the patient is sitting or standing upright and breathing normally through the mouthpiece of the nebulizer. Nose clips may help the patient breathe through the mouth.

Instruct patients on multiple therapies to take their medications, prior to inhaling TOBI or as directed by their physician.

TOBI should not be used if it is cloudy, if there are particles in the solution, or if it has been stored at room temperature for more than 28 days.

3 DOSAGE FORMS AND STRENGTHS

TOBI is supplied as a sterile inhalational solution for nebulization in single-dose 5 mL ampoules. Each 5 mL ampoule contains 300 mg of tobramycin.

4 CONTRAINDICATIONS

TOBI is contraindicated in patients with a known hypersensitivity to any aminoglycoside.

5 WARNINGS AND PRECAUTIONS

5.1 Bronchospasm

Bronchospasm can occur with inhalation of TOBI. In clinical studies with TOBI, changes in FEV1 measured after the inhaled dose were similar in tobramycin inhalation solution and placebo groups. Bronchospasm that occurs during the use of TOBI should be treated as medically appropriate.

5.2 Ototoxicity

Ototoxicity with use of TOBI

Ototoxicity, manifested as both auditory and vestibular toxicity, has been reported with parenteral aminoglycosides.

Transient tinnitus occurred in eight TOBI treated patients versus no placebo patients in the clinical studies. Tinnitus may be a sentinel symptom of ototoxicity, and therefore the onset of this symptom warrants further clinical investigation. Ototoxicity, as measured by complaints of hearing loss or by audiometric evaluations, did not occur with TOBI therapy during clinical studies, however in postmarketing experience, patients receiving TOBI have reported hearing loss. Vestibular toxicity may be manifested by vertigo, ataxia or dizziness. Patients with known or suspected auditory or vestibular dysfunction should be closely monitored when taking TOBI. Monitoring might include obtaining audiometric evaluations and serum tobramycin levels. If ototoxicity is noted, the patient should be managed as medically appropriate, including potentially discontinuing TOBI.

Risk of Ototoxicity Due to Mitochondrial DNA Variants

Cases of ototoxicity with aminoglycosides have been observed in patients with certain variants in the mitochondrially encoded 12S rRNA gene (MT-RNR1), particularly the m.1555A>G variant. Ototoxicity occurred in some patients even when their aminoglycoside serum levels were within the recommended range. Mitochondrial DNA variants are present in less than 1% of the general US population, and the proportion of the variant carriers who may develop ototoxicity as well as the severity of ototoxicity is unknown. In case of known maternal history of ototoxicity due to aminoglycoside use or a known mitochondrial DNA variant in the patient, consider alternative treatments other than aminoglycosides unless the increased risk of permanent hearing loss is outweighed by the severity of infection and lack of safe and effective alternative therapies.

5.3 Nephrotoxicity

Nephrotoxicity was not seen during clinical studies with TOBI but has been associated with aminoglycosides as a class. Patients with known or suspected renal dysfunction or taking concomitant nephrotoxic drugs along with TOBI should have serum concentrations of tobramycin and laboratory measurements of renal function obtained at the discretion of the treating physician. If nephrotoxicity develops, the patient should be managed as medically appropriate, including potentially discontinuing TOBI.

5.4 Neuromuscular Disorders

Aminoglycosides, including tobramycin, may aggravate muscle weakness because of a potential curare-like effect on neuromuscular function. Neuromuscular blockade, respiratory failure, and prolonged respiratory paralysis may occur more commonly in patients with underlying neuromuscular disorders, such as myasthenia gravis or Parkinson’s disease. Prolonged respiratory paralysis may also occur in patients receiving concomitant neuromuscular blocking agents. If neuromuscular blockade occurs, it may be reversed by the administration of calcium salts but mechanical assistance may be necessary.

5.5 Embryo-fetal Toxicity

Aminoglycosides can cause fetal harm when administered to a pregnant woman. Aminoglycosides cross the placenta, and streptomycin has been associated with several reports of total, irreversible, bilateral congenital deafness in pediatric patients exposed in utero. However, systemic absorption of tobramycin following inhaled administration is expected to be minimal [see Clinical Pharmacology (12.3)]. Patients who use TOBI during pregnancy, or become pregnant while taking TOBI should be apprised of the potential hazard to the fetus [see Use in Specific Populations (8.1)].

5.6 Concomitant Use of Systemic Aminoglycosides

Patients receiving concomitant TOBI and parenteral aminoglycoside therapy should be monitored as clinically appropriate for toxicities associated with aminoglycosides as a class. Serum tobramycin levels should be monitored.

6 ADVERSE REACTIONS

The following serious adverse reactions are described below and elsewhere in the labeling:

- Bronchospasm [see Warnings and Precautions (5.1)]
- Ototoxicity [see Warnings and Precautions (5.2)]
- Nephrotoxicity [see Warnings and Precautions (5.3)]
- Neuromuscular Disorders [see Warnings and Precautions (5.4)]
- Embryo-fetal Toxicity [see Warnings and Precautions (5.5)]
- Concomitant Use of Systemic Aminoglycosides [see Warnings and Precautions (5.6)]

6.1 Clinical Trials Experience

Because clinical trials are conducted under widely varying conditions, adverse reaction rates observed in the clinical trials of a drug cannot be directly compared to rates in the clinical trials of another drug and may not reflect the rates observed in practice.

TOBI was studied in two Phase 3 clinical studies involving 258 cystic fibrosis patients ranging in age from 6 to 48 years. Patients received TOBI in alternating periods of 28 days on and 28 days off drug in addition to their standard cystic fibrosis therapy for a total of 24 weeks.

Table 1 lists the percent of patients with selected adverse reactions that occurred in >5% of TOBI patients during the two Phase 3 studies.

Table 1: Percent of Patients With Selected Adverse Reactions Occurring in >5% of TOBI Patients
Adverse Reaction | Tobramycin Inhalation Solution; (n = 258); % | Placebo; (n = 262); %
Cough Increased | 46.1 | 47.3
Pharyngitis | 38.0 | 39.3
Sputum Increased | 37.6 | 39.7
Dyspnea | 33.7 | 38.5
Hemoptysis | 19.4 | 23.7
Lung Function Decreased [Includes reported decreases in pulmonary function tests or decreased lung volume on chest radiograph associated with intercurrent illness or study drug administration.] | 16.3 | 15.3
Voice Alteration | 12.8 | 6.5
Taste Perversion | 6.6 | 6.9
Rash | 5.4 | 6.1

Selected adverse reactions that occurred in less than or equal to 5% of patients treated with TOBI:

Ear and Labyrinth Disorders: Tinnitus

Musculoskeletal and Connective Tissue Disorders: Myalgia

Infections and Infestations: Laryngitis

Voice alteration and tinnitus were the only adverse reactions reported by significantly more TOBI-treated patients. Thirty-three patients (13%) treated with TOBI complained of voice alteration compared to 17 (7%) placebo patients. Voice alteration was more common in the on-drug periods.

Eight patients from the TOBI group (3%) reported tinnitus compared to no placebo patients. All episodes were transient, resolved without discontinuation of the TOBI treatment regimen, and were not associated with loss of hearing in audiograms. Tinnitus is one of the sentinel symptoms of cochlear toxicity, and patients with this symptom should be carefully monitored for high frequency hearing loss. The numbers of patients reporting vestibular adverse experiences such as dizziness were similar in the TOBI and placebo groups.

Changes in Serum Creatinine

Nine (3%) patients in the TOBI group and nine (3%) patients in the placebo group had increases in serum creatinine of at least 50% over baseline. In all nine patients in the TOBI group, creatinine decreased at the next visit.

6.2 Postmarketing Experience

The following adverse reactions have been identified during post-approval use of TOBI. Because these reactions are reported voluntarily from a population of uncertain size, it is not always possible to reliably estimate their frequency or establish a causal relationship to drug exposure.

Ear and Labyrinth Disorders

Hearing loss: Some of these reports occurred in patients with previous or concomitant treatment with systemic aminoglycosides. Patients with hearing loss frequently reported tinnitus [see Warnings and Precautions (5.2)].

Skin and Subcutaneous Tissue Disorders

Hypersensitivity, pruritus, urticaria, rash

Nervous System Disorders

Aphonia, dysgeusia

Respiratory, Thoracic, and Mediastinal Disorders

Bronchospasm [see Warnings and Precautions (5.1)] oropharyngeal pain

Metabolism and Nutrition Disorders

Decreased appetite

7 DRUG INTERACTIONS

7.1 Drugs with Neurotoxic, Nephrotoxic or Ototoxic Potential

Concurrent and/or sequential use of TOBI with other drugs with neurotoxic, nephrotoxic, or ototoxic potential should be avoided.

7.2 Diuretics

Some diuretics can enhance aminoglycoside toxicity by altering aminoglycoside concentrations in serum and tissue. TOBI should not be administered concomitantly with ethacrynic acid, furosemide, urea, or intravenous mannitol. The interaction between inhaled mannitol and TOBI has not been evaluated.

8 USE IN SPECIFIC POPULATIONS

8.1 Pregnancy

Risk Summary

Aminoglycosides can cause fetal harm. Published literature reports that use of streptomycin, an aminoglycoside, can cause total, irreversible, bilateral congenital deafness when administered to a pregnant woman [see Warnings and Precautions (5.5)]. Although there are no available data on TOBI use in pregnant women to inform a drug-associated risk of major birth defects, miscarriage or adverse maternal or fetal outcomes, systemic absorption of tobramycin following inhaled administration is expected to be minimal [see Clinical Pharmacology (12.3)]. There are risks to the mother associated with cystic fibrosis in pregnancy (see Clinical Considerations). In animal reproduction studies with subcutaneous administration of tobramycin in pregnant rats and rabbits during organogenesis, there were no adverse developmental outcomes; however, ototoxicity was not evaluated in the offspring from these studies (see Data). Advise pregnant women of the potential risk to a fetus.

The estimated background risk of major birth defects and miscarriage for the indicated populations are unknown. All pregnancies have a background risk of birth defect, loss, or other adverse outcomes. In the U.S. general population, the estimated background risk of major birth defects and miscarriage in clinically recognized pregnancies is 2% to 4% and 15% to 20%, respectively.

Clinical Considerations

Disease-Associated Maternal and/or Embryo/Fetal Risk

Cystic fibrosis may increase the risk for preterm delivery.

Data

Animal Data

No reproductive toxicity studies have been conducted with TOBI (tobramycin administered by inhalation). However, subcutaneous administration of tobramycin at doses of up to 100 (rat) or 20 (rabbit) mg/kg/day during organogenesis was not associated with adverse developmental outcomes. Doses of tobramycin ≥40 mg/kg/day were severely maternally toxic to rabbits and precluded the evaluation of adverse developmental outcomes. Ototoxicity was not evaluated in offspring during non-clinical reproductive toxicity studies with tobramycin.

8.2 Lactation

Risk Summary

There are no data on the presence of TOBI in either human or animal milk, the effects on the breastfed infant, or the effects on milk production. Limited published data on other formulations of tobramycin in lactating women indicate that tobramycin is present in human milk. However, systemic absorption of tobramycin following inhaled administration is expected to be minimal [see Clinical Pharmacology (12.3)]. Tobramycin may cause alteration in the intestinal flora of the breastfeeding infant (see Clinical Considerations). The developmental and health benefits of breastfeeding should be considered along with the mother's clinical need for TOBI and any potential adverse effects on the breastfed infant from TOBI or from the underlying maternal condition.

Clinical Considerations

Tobramycin may cause intestinal flora alteration. Advise a woman to monitor the breastfed infant for loose or bloody stools and candidiasis (thrush, diaper rash).

8.4 Pediatric Use

The safety and efficacy of TOBI in pediatric patients under 6 years of age has not been established. The use of TOBI is not indicated in children <6 years of age [see Indications and Usage (1) and Dosage and Administration (2)].

8.5 Geriatric Use

Clinical studies of TOBI did not include patients aged 65 years and over. Tobramycin is known to be substantially excreted by the kidney, and the risk of adverse reactions to this drug may be greater in patients with impaired renal function. Because elderly patients are more likely to have decreased renal function, it may be useful to monitor renal function [see Warnings and Precautions (5.3)].

10 OVERDOSAGE

Signs and symptoms of acute toxicity from overdosage of intravenous (IV) tobramycin might include dizziness, tinnitus, vertigo, loss of high-tone hearing acuity, respiratory failure, neuromuscular blockade, and renal impairment. Administration by inhalation results in low systemic bioavailability of tobramycin. Tobramycin is not significantly absorbed following oral administration. Tobramycin serum concentrations may be helpful in monitoring overdosage.

Acute toxicity should be treated with immediate withdrawal of TOBI, and baseline tests of renal function should be undertaken.

In all cases of suspected overdosage, physicians should contact the Regional Poison Control Center for information about effective treatment. In the case of any overdosage, the possibility of drug interactions with alterations in drug disposition should be considered.

Hemodialysis may be helpful in removing tobramycin from the body.

11 DESCRIPTION

TOBI® is a tobramycin solution for inhalation. It is a sterile, clear, slightly yellow, non-pyrogenic, aqueous solution with the pH and salinity adjusted specifically for administration by a compressed air driven reusable nebulizer. The chemical formula for tobramycin is C18H37N5O9 and the molecular weight is 467.52 g/mol. Tobramycin is O-3-amino-3-deoxy-α-D‑glucopyranosyl-(1→4)-O-[2,6-diamino-2,3,6- trideoxy-α-D-ribo-hexopyranosyl-(1→6)]-2-deoxy-L-streptamine. The structural formula for tobramycin is:

Each single-dose 5 mL ampoule contains 300 mg tobramycin and 11.25 mg sodium chloride in sterile water for injection. Sulfuric acid and sodium hydroxide are added to adjust the pH to 6.0. Nitrogen is used for sparging. All ingredients meet USP requirements. The formulation contains no preservatives.

12 CLINICAL PHARMACOLOGY

12.1 Mechanism of Action

Tobramycin is an aminoglycoside antibacterial [see Microbiology (12.4)].

12.3 Pharmacokinetics

Absorption

TOBI contains tobramycin, a cationic polar molecule that does not readily cross epithelial membranes.(1) The bioavailability of TOBI may vary because of individual differences in nebulizer performance and airway pathology.(2) Following administration of TOBI, tobramycin remains concentrated primarily in the airways.

Serum Concentrations

The average serum concentration of tobramycin one hour after inhalation of a single 300-mg dose of TOBI by cystic fibrosis patients was 0.95 mcg/mL. After 20 weeks of therapy on the TOBI regimen, the average serum tobramycin concentration one hour after dosing was 1.05 mcg/mL.

Sputum Concentrations

Ten minutes after inhalation of the first 300-mg dose of TOBI by cystic fibrosis patients, the average concentration of tobramycin was 1237 mcg/g (range 35 to 7417 mcg/g) in sputum. Tobramycin does not accumulate in sputum; after 20 weeks of therapy with the TOBI regimen, the average concentration of tobramycin at ten minutes after inhalation was 1154 mcg/g (range 39 to 8085 mcg/g) in sputum. Two hours after inhalation, sputum concentrations declined to approximately 14% of tobramycin levels at ten minutes after inhalation.

Distribution

Following administration of TOBI, tobramycin remains concentrated primarily in the airways. Binding of tobramycin to serum proteins is negligible.

Elimination

Metabolism

Tobramycin is not metabolized.

Excretion

The elimination half-life of tobramycin from serum is approximately 2 and 3 hours after intravenous (IV) administration and inhalation, respectively. Systemically absorbed tobramycin is primarily excreted unchanged in the urine principally by glomerular filtration. Unabsorbed tobramycin, following TOBI administration, is probably eliminated primarily in expectorated sputum.

12.4 Microbiology

Mechanism of Action

Tobramycin is an aminoglycoside antibacterial produced by Streptomyces tenebrarius.(^1) It acts primarily by disrupting protein synthesis, leading to altered cell membrane permeability, progressive disruption of the cell envelope, and eventual cell death.(^3)

Tobramycin has in vitro activity against gram-negative bacteria including Pseudomonas aeruginosa. It is bactericidal in vitro at concentrations equal to or slightly greater than the minimum inhibitory concentration (MIC).

Resistance

Treatment for 6 months with TOBI in two clinical studies did not affect the susceptibility of the majority of P. aeruginosa isolates tested; however, increased minimum inhibitory concentrations (MICs) were noted in some patients. The clinical significance of this information has not been clearly established in the treatment of P. aeruginosa in cystic fibrosis patients [see Clinical Studies (14)].

Susceptibility Test Methods

Interpretive criteria for inhaled antibacterial products are not defined. The in vitro antimicrobial susceptibility test methods used for parenteral tobramycin therapy can be used to monitor the susceptibility of P. aeruginosa isolated from cystic fibrosis patients. If decreased susceptibility is noted, the results should be reported to the clinician.

Susceptibility breakpoints established for parenteral administration of tobramycin do not apply to aerosolized administration of TOBI. The relationship between in vitro susceptibility test results and clinical outcome with TOBI therapy is not clear.

A single sputum sample from a cystic fibrosis patient may contain multiple morphotypes of Pseudomonas aeruginosa and each morphotype may have a different level of in vitro susceptibility to tobramycin.

13 NONCLINICAL TOXICOLOGY

13.1 Carcinogenesis, Mutagenesis, Impairment of Fertility

A two-year rat inhalation toxicology study to assess carcinogenic potential of TOBI has been completed. Rats were exposed to TOBI for up to 1.5 hours per day for 95 weeks. The clinical formulation of the drug was used for this carcinogenicity study. Serum levels of tobramycin of up to 35 mcg/mL were measured in rats, in contrast to the average 1 mcg/mL levels observed in cystic fibrosis patients in clinical trials. There was no drug-related increase in the incidence of any variety of tumor.

Additionally, tobramycin has been evaluated for genotoxicity in a battery of in vitro and in vivo tests. The Ames bacterial reversion test, conducted with 5 tester strains, failed to show a significant increase in revertants with or without metabolic activation in all strains. Tobramycin was negative in the mouse lymphoma forward mutation assay, did not induce chromosomal aberrations in Chinese hamster ovary cells, and was negative in the mouse micronucleus test.

Subcutaneous administration of up to 100 mg/kg of tobramycin did not affect mating behavior or cause impairment of fertility in male or female rats.

14 CLINICAL STUDIES

Two identically designed, double-blind, randomized, placebo-controlled, parallel group, 24-week clinical studies (Study 1 and Study 2) at a total of 69 cystic fibrosis centers in the United States were conducted in cystic fibrosis patients with P. aeruginosa. Subjects who were less than 6 years of age, had a baseline creatinine of >2 mg/dL, or had Burkholderia cepacia isolated from sputum were excluded.

All subjects had baseline FEV1 % predicted between 25% and 75%. In these clinical studies, 258 patients received TOBI therapy on an outpatient basis (see Table 2) using a hand-held PARI LC PLUS Reusable Nebulizer with a DeVilbiss Pulmo-Aide compressor.

Table 2: Dosing Regimens in Clinical Studies
 | Cycle 1 |  | Cycle 2 |  | Cycle 3
 | 28 days | 28 days | 28 days | 28 days | 28 days | 28 days
TOBI | TOBI | No drug | TOBI | No drug | TOBI | No drug
regimen | 300 mg |  | 300 mg |  | 300 mg
n = 258 | twice daily |  | twice daily |  | twice daily
Placebo | placebo | No drug | placebo | No drug | placebo | No drug
regimen | twice daily |  | twice daily |  | twice daily
n = 262

All patients received either TOBI or placebo (saline with 1.25 mg quinine for flavoring) in addition to standard treatment recommended for cystic fibrosis patients, which included oral and parenteral antipseudomonal therapy, β2-agonists, cromolyn, inhaled steroids, and airway clearance techniques. In addition, approximately 77% of patients were concurrently treated with dornase alfa (PULMOZYME, Genentech).

In each study, TOBI-treated patients experienced significant improvement in pulmonary function. Improvement was demonstrated in the TOBI group in Study 1 by an average increase in FEV1 % predicted of about 11% relative to baseline (Week 0) during 24 weeks compared to no average change in placebo patients. In Study 2, TOBI-treated patients had an average increase of about 7% compared to an average decrease of about 1% in placebo patients. Figure 1 shows the average relative change in FEV1 % predicted over 24 weeks for both studies.

Figure 1: Relative Change From Baseline in FEV1% Predicted

In each study, TOBI therapy resulted in a significant reduction in the number of P. aeruginosa colony forming units (CFUs) in sputum during the on-drug periods. Sputum bacterial density returned to baseline during the off-drug periods. Reductions in sputum bacterial density were smaller in each successive cycle (see Figure 2).

Figure 2: Absolute Change From Baseline in Log10 CFUs

Patients treated with TOBI were hospitalized for an average of 5.1 days compared to 8.1 days for placebo patients. Patients treated with TOBI required an average of 9.6 days of parenteral antipseudomonal, antibacterial treatment compared to 14.1 days for placebo patients. During the 6 months of treatment, 40% of TOBI patients and 53% of placebo patients were treated with parenteral antipseudomonal antibacterials.

The relationship between in vitro susceptibility test results and clinical outcome with TOBI therapy is not clear. However, four TOBI patients who began the clinical trial with P. aeruginosa isolates having MIC values ≥128 mcg/mL did not experience an improvement in FEV1 or a decrease in sputum bacterial density.

Treatment with TOBI did not affect the susceptibility of the majority of P. aeruginosa isolates during the 6-month studies. However, some P. aeruginosa isolates did exhibit increased tobramycin MICs. The percentage of patients with P. aeruginosa isolates with tobramycin MICs ≥16 mcg/mL was 13% at the beginning, and 23% at the end of 6 months of the TOBI regimen.

15 REFERENCES

1. Neu HC. Tobramycin: an overview. [Review]. J Infect Dis 1976; Suppl 134:S3-19.
2. Weber A, Smith A, Williams-Warren J et al. Nebulizer delivery of tobramycin to the lower respiratory tract. Pediatr Pulmonol 1994; 17 (5):331-9.
3. Bryan LE. Aminoglycoside resistance. Bryan LE, Ed. Antimicrobial drug resistance. Orlando, FL: Academic Press, 1984: 241-77.

16 HOW SUPPLIED/STORAGE AND HANDLING

16.1 How Supplied

TOBI is supplied as a sterile, clear, slightly yellow, non-pyrogenic, aqueous solution packaged in a 5 mL single-dose ampoule (300 mg tobramycin) for nebulization.

TOBI 300 mg is available as follows:

5 mL single-dose ampoule (carton of 56) NDC 49502-345-73

16.2 Storage and Handling

TOBI should be stored under refrigeration at 2ºC–8ºC/36ºF–46ºF. Upon removal from the refrigerator, or if refrigeration is unavailable, TOBI pouches (opened or unopened) may be stored at room temperature (up to 25ºC/77ºF) for up to 28 days. TOBI should not be used beyond the expiration date stamped on the ampoule when stored under refrigeration (2ºC–8ºC/36ºF–46ºF) or beyond 28 days when stored at room temperature (25ºC/77ºF).

TOBI ampoules should not be exposed to intense light. The solution in the ampoule is slightly yellow, but may darken with age if not stored in the refrigerator; however, the color change does not indicate any change in the quality of the product as long as it is stored within the recommended storage conditions.

17 PATIENT COUNSELING INFORMATION

Advise the patient to read the FDA-approved patient labeling (Patient Information and Instructions for Use).

Difficulty Breathing:

Advise patients to inform their physicians if they experience shortness of breath or wheezing after administration of tobramycin inhalation solution. Tobramycin inhalation solution can cause a narrowing of the airway [see Warnings and Precautions (5.1)].

Hearing Loss:

Advise patients to inform their physician if they experience ringing in the ears, dizziness, or any changes in hearing because tobramycin inhalation solution has been associated with hearing loss [see Warnings and Precautions (5.2)].

Kidney Damage:

Advise patients to inform their physician if they have any history of kidney problems because tobramycin inhalation solution is in a class of drugs that have caused kidney damage [see Warnings and Precautions (5.3)].

Embryo-fetal Toxicity:

Advise pregnant women that aminoglycosides can cause irreversible congenital deafness when administered to a pregnant woman [see Warnings and Precautions (5.5) and Use in Specific Populations (8.1)].

Lactation:

Advise a woman to monitor their breastfed infants for diarrhea and/or bloody stools [see Use in Specific Populations (8.2)].

Manufactured for:
Mylan Specialty L.P.
Morgantown, WV 26505 U.S.A.

Manufactured by:
Woodstock Sterile Solutions, Inc.
Woodstock, IL 60098 U.S.A.

© 2023 Viatris Inc.

TOBI is a registered trademark of BGP Products Operations GmbH, a Viatris Company.

The brands listed are trademarks of their respective owners.

WS:TOBRIS:R2

PATIENT INFORMATION

TOBI (TOH-bee)

(tobramycin inhalation solution)

for oral inhalation use

What is TOBI?

TOBI is a prescription medicine that is used to treat people with cystic fibrosis who have a bacterial infection called Pseudomonas aeruginosa. TOBI contains an antibacterial medicine called tobramycin (an aminoglycoside).

It is not known if TOBI is safe and effective:

- in children under 6 years of age
- in people who have an FEV1 less than 25% or greater than 75% predicted
- in people who are colonized with a bacterium called Burkholderia cepacia

Do not take TOBI if you are allergic to tobramycin, any of the ingredients in TOBI, or to any other aminoglycoside antibacterial.

See the end of this Patient Information for a complete list of ingredients in TOBI.

Before you take TOBI, tell your healthcare provider about all of your medical conditions, including if you:

- have or have had hearing problems (including noises in your ears such as ringing or hissing), hearing loss, or your mother has had hearing problems after taking an aminoglycoside.
- have been told you have certain gene variants (a change in the gene) related to hearing abnormalities inherited from your mother.
- have dizziness
- have or have had kidney problems
- have or have had problems with muscle weakness such as myasthenia gravis or Parkinson’s disease
- have or have had breathing problems such as wheezing, coughing, or chest tightness
- are pregnant or plan to become pregnant. TOBI is in a class of drugs that can harm your unborn baby.
- are breastfeeding or plan to breastfeed. It is not known if TOBI passes into your breast milk.
- are receiving aminoglycoside therapy by injection or through a vein (intravenous) while taking TOBI. Your blood levels of tobramycin will be checked.

Tell your healthcare provider about all the medicines you take, including prescription medicines, over-the-counter medicines, vitamins, and herbal supplements.

How should I take TOBI?

- See the step-by-step Instructions for Use about the right way to take your TOBI.
- Take TOBI exactly as your healthcare provider tells you. Do not change your dose or stop taking TOBI unless your healthcare provider tells you to.
- The usual dose for adults and children over 6 years of age is:
  - 1 single-use ampule of TOBI inhaled 2 times each day using a hand-held PARI LC PLUS™ Reusable Nebulizer and a DeVilbiss® Pulmo-Aide® air compressor.
- Each dose of TOBI should be taken as close to 12 hours apart as possible.
- You should not take your dose less than 6 hours apart.
- TOBI is taken as a breathing treatment (inhalation) with a hand-held PARI LC PLUS Reusable Nebulizer with a DeVilbiss Pulmo-Aide compressor. Do not use any other nebulizer for your TOBI treatment.
- Do not mix or dilute TOBI with dornase alfa or other medicines in your nebulizer system.
- Each treatment should take about 15 minutes.
- TOBI should be inhaled while you are sitting or standing upright and breathing normally through the mouthpiece of the nebulizer. Nose clips may help you to breathe through your mouth.
- If you forget to take TOBI and there are at least 6 hours to your next dose, take your dose as soon as you can. Otherwise, wait for your next dose. Do not double the dose to make up for the missed dose.
- After using TOBI for 28 days, you should stop using it and wait 28 days. After you have stopped using TOBI for 28 days, you should start using TOBI again for 28 days. Complete the full 28-day course even if you are feeling better. It is important that you keep to the 28-day on, 28-day off cycle.

If you are taking several medicines or treatments to treat your cystic fibrosis, you should take your medicines or other treatments before inhaling TOBI or as directed by your healthcare provider. Tell your healthcare provider about all the medicines you take, including prescription and over-the-counter prescription medicines, vitamins, and herbal supplements.

Using TOBI with certain other medicines can cause serious side effects.

If you are using TOBI, you should discuss with your healthcare provider if you should take:

- other medicines that may harm your nervous system, kidneys, or hearing
- “water pills” (diuretics) such as ethacrynic acid, furosemide, or intravenous mannitol
- urea

Ask your healthcare provider or pharmacist for a list of these medicines, if you are not sure.

Know the medicines you take. Keep a list of them and show it to your healthcare provider and pharmacist when you get a new medicine.

What are the possible side effects of TOBI?

TOBI may cause serious side effects, including:

- severe breathing problems (bronchospasm). Tell your healthcare provider right away if you get any of these symptoms of bronchospasm with using TOBI:
  - shortness of breath with wheezing
  - coughing and chest tightness
- hearing loss or ringing in the ears (ototoxicity). Tell your healthcare provider right away if you have hearing loss or you hear noises in your ears such as ringing or hissing. Tell your healthcare provider if you develop vertigo, difficulty with balance or dizziness.
- worsening kidney problems (nephrotoxicity). TOBI is in a class of drugs which may cause worsening kidney problems, especially in people with known or suspected kidney problems. Your healthcare provider may do a blood test to check how your kidneys are working while you are using TOBI.
- worsening muscle weakness (neuromuscular disorder). TOBI is in a class of drugs which can cause muscle weakness to get worse in people who already have problems with muscle weakness (myasthenia gravis or Parkinson’s disease).

The most common side effects of TOBI include:

- increased cough
- coughing up blood
- voice changes

- sore throat
- decreased lung function
- loss or change in taste

- increased sputum
- trouble breathing
- rash

These are not all of the possible side effects of TOBI.

Call your doctor for medical advice about side effects. You may report side effects to FDA at 1-800-FDA-1088.

General information about the safe and effective use of TOBI

Medicines are sometimes prescribed for purposes other than those listed in a Patient Information leaflet. Do not use TOBI for a condition for which it was not prescribed. Do not give it to other people, even if they have the same symptoms you have. It may harm them. You can ask your pharmacist or healthcare provider for more information about TOBI that is written for health professionals.

What are the ingredients in TOBI?

Active ingredient: tobramycin

Inactive ingredients: sodium chloride in sterile water for injection, sulfuric acid, sodium hydroxide, and nitrogen

What is Pseudomonas aeruginosa?

It is a very common bacterium that infects the lungs of nearly everyone with cystic fibrosis at some time during their lives. Some people do not get this infection until later in their lives, while others get it very young. It is one of the most damaging bacteria for people with cystic fibrosis. If the infection is not properly managed, it will continue to damage your lungs causing further problems to your breathing.

Manufactured for: Mylan Specialty L.P., Morgantown, WV 26505 U.S.A.

For more information, call Mylan at 1-877-446-3679 (1-877-4-INFO-RX).

This Patient Information has been approved by the U.S. Food and Drug Administration. Revised: 2/2023

© 2023 Viatris Inc.

TOBI is a registered trademark of BGP Products Operations GmbH, a Viatris Company.

The brands listed are trademarks of their respective owners.

WS:PIL:TOBRIS:R2

Instructions for Use

TOBI (TOH-bee)
(tobramycin inhalation solution)
for oral inhalation use

Read this Instructions for Use before you start using TOBI inhalation solution and each time you get a refill. There may be new information. This leaflet does not take the place of talking to your healthcare provider about your medical condition or treatment.

TOBI is made for inhalation using a PARI LC PLUS™ Reusable Nebulizer and a DeVilbiss® Pulmo-Aide® air compressor. TOBI can be taken at home, school, or at work. The following instructions tell you how to use the DeVilbiss Pulmo-Aide air compressor and PARI LC PLUS Reusable Nebulizer to administer TOBI.

You will need the following supplies (See Figure A):

- 1 TOBI plastic ampule (TOBI is packaged with 4 ampules in each foil pouch)
- DeVilbiss Pulmo-Aide air compressor
- PARI LC PLUS Reusable Nebulizer
- Tubing to connect the nebulizer and compressor
- Clean paper or cloth towels
- Nose clips (optional)

(Figure A)

It is important that your nebulizer and compressor function properly before starting your TOBI therapy.

Note: Read the manufacturer care and use instructions for important information.

Prepare Your TOBI for Inhalation Therapy

Step 1: Wash your hands thoroughly with soap and water.

Step 2: Open the foil pouch.

Step 3: Separate 1 TOBI ampule by gently pulling apart at the bottom tabs (See Figure B). Place the remaining TOBI ampules in the refrigerator.

(Figure B)

Step 4: Check the expiration date stamped on the TOBI ampule (See Figure C). Do not use the TOBI ampule if the expiration date has passed.

(Figure C)

Step 5: Check that the TOBI ampule medicine is clear and does not have particles.

- Unrefrigerated TOBI, which is normally slightly yellow, may darken with age. This color change does not mean there is any change in the quality of the medicine.
- Do not use the TOBI ampule if the medicine is cloudy or has particles.
- Throw it away and get a new one.

Step 6: Lay out the parts of a PARI LC PLUS Reusable Nebulizer package on a clean, dry paper or cloth towel. You should have the following parts (See Figure D):

- Nebulizer Top and Bottom (Nebulizer Cup) Assembly
- Inspiratory Valve Cap
- Mouthpiece with Valve
- Tubing

(Figure D)

Step 7: Remove the Nebulizer Top from the Nebulizer Cup by twisting the Nebulizer Top counter-clockwise, and then lifting off (See Figure E).

(Figure E)

Step 8: Place the Nebulizer Top on the clean paper or cloth towel by standing the Nebulizer Cup upright on the towel (See Figure F).

(Figure F)

Step 9: Connect one end of the tubing to the compressor air outlet (See Figure G). The tubing should fit tightly.

(Figure G)

Step 10: Plug in your compressor to an electrical outlet (See Figure H).

(Figure H)

Step 11: Open the TOBI ampule by holding the bottom tab with 1 hand and twisting off the top of the TOBI ampule with the other hand (See Figure I). Be careful not to squeeze the TOBI ampule until you are ready to empty all the medicine into the Nebulizer Cup.

(Figure I)

Step 12: Squeeze all the medicine of the TOBI ampule into the Nebulizer Cup (See Figure J).

(Figure J)

Step 13: Replace the Nebulizer Top. To replace the Nebulizer Top insert the Nebulizer Top into the Nebulizer Cup with the semi-circle halfway down the stem of the Nebulizer Top facing the Nebulizer Outlet. Turn the Nebulizer Top clockwise until securely fastened to the nebulizer Cup. (See Figure K).

(Figure K)

Step 14: Push the Mouthpiece straight onto the Nebulizer Outlet (See Figure L).

(Figure L)

Step 15: Firmly push the Inspiratory Valve Cap straight down onto the Nebulizer Top (See Figure M). The Inspiratory Valve Cap will fit tightly.

(Figure M)

Step 16: Hold the Nebulizer Cup upright and firmly push the free end of the tubing from the compressor to the Air Intake on the bottom of the Nebulizer Cup (See Figure N). Make sure to keep the Nebulizer Cup upright.

(Figure N)

Giving your TOBI Inhalation Therapy

Step 17: Turn on the compressor (See Figure O).

(Figure O)

Step 18: Check for a steady mist from the Mouthpiece (See Figure P). If there is no mist, check all tubing connections and make sure that the compressor is working properly.

(Figure P)

Step 19: Sit or stand in an upright position that will allow you to breathe normally. Place the Mouthpiece between your teeth and on top of your tongue and breathe normally only through your mouth (See Figure Q). Nose clips may help you breathe through your mouth and not through your nose. Do not block the airflow with your tongue.

(Figure Q)

Step 20: Keep breathing in your TOBI medicine for at least 15 minutes to get your full dose. Continue therapy until all your TOBI medicine is gone, and there is no longer any mist being made. You may hear a sputtering sound coming from the Mouthpiece when the Nebulizer Cup is empty. The entire TOBI therapy should take about 15 minutes to complete.

If you are interrupted, need to cough or rest during your TOBI treatment, turn off the compressor to save your medicine. Turn the compressor back on when you are ready to restart your treatment.

Follow the nebulizer cleaning and disinfecting instructions after completing your therapy.

After your TOBI Inhalation Therapy

Cleaning Your Nebulizer

To reduce the risk of infection, illness or injury from contamination, you must thoroughly clean all parts of the nebulizer as instructed after each treatment. Never use a nebulizer with a clogged nozzle. If the nozzle is clogged, no aerosol mist is made, and your therapy will not be as effective. Replace the nebulizer if clogging occurs.

1) Remove tubing from nebulizer and disassemble nebulizer parts.

2) Wash all parts (except tubing) with warm water and liquid dish soap.

3) Rinse thoroughly with warm water and shake out water.

4) Air dry or hand dry nebulizer parts on a clean, lint-free cloth. Reassemble nebulizer when dry, and store.

You can also wash all parts of the nebulizer in a dishwasher (except tubing).

1) Place the nebulizer parts in a dishwasher basket.

2) Place the dishwasher basket on the top rack of the dishwasher.

3) Remove and dry the parts when the cycle is complete.

Disinfecting Your Nebulizer

Your nebulizer is for your use only. Do not share your nebulizer with other people. You must disinfect the nebulizer every other treatment day. Failure to disinfect the nebulizer every other treatment day could lead to serious or fatal illness.

Clean the nebulizer as described above. Every other treatment day, disinfect the nebulizer parts (except tubing) by boiling them in water for a full 10 minutes. Dry parts on a clean, lint-free cloth.

Care and Use of Your Pulmo-Aide Compressor

Follow the manufacturer instructions for care and use of your compressor.

Filter Change:

- DeVilbiss Compressor filters should be changed every 6 months or sooner if the filter turns completely gray in color.

Compressor Cleaning:

- With power switch in the “Off” position, unplug power cord from wall outlet.
- Wipe outside of the compressor cabinet with a clean, damp cloth every few days to keep dust free.

Caution: Do not submerge in water because this will damage the compressor.

How should I store TOBI?

- Store TOBI ampules in a refrigerator between 36°F to 46°F (2°C to 8°C) until needed.
- You may store the TOBI ampules in the foil pouches (opened or unopened) at room temperature 77°F (25°C) for up to 28 days.
- Do not use TOBI ampules if they have been stored at room temperature for more than 28 days.
- Protect TOBI ampules from light.

Keep TOBI and all medicines out of the reach of children.

This Instructions for Use has been approved by the U.S. Food and Drug Administration.

Additional Information

Nebulizer: 1-800-327-8632

Compressor: 1-800-338-1988

TOBI: Call Mylan at 1-877-446-3679 (1-877-4-INFO-RX).

Manufactured for:
Mylan Specialty L.P.
Morgantown, WV 26505 U.S.A.

Manufactured by:
Woodstock Sterile Solutions, Inc.
Woodstock, IL 60098 U.S.A.

© 2023 Viatris Inc.

TOBI is a registered trademark of BGP Products Operations GmbH, a Viatris Company.

The brands listed are trademarks of their respective owners.

WS:IFU:TOBRIS:R2

Revised: 2/2023

PRINCIPAL DISPLAY PANEL – 300 mg / 5 mL Ampules

NDC 49502-345-73

TOBI®
Tobramycin Inhalation Solution, USP

300 mg / 5 mL Ampules
56 Single-Use Ampules (28-Day Supply)

Rx only

Store In Refrigerator

Contents: Each foil pouch contains four sterile, non-pyrogenic, single-use ampules. Each 5 mL ampule contains one 300 mg dose of Tobramycin, USP and 11.25 mg Sodium Chloride in Sterile Water for Injection.

Dosage and Administration: Each single-use ampule contains one 300 mg dose.

For inhalation only using required type of nebulizer. See package insert for full prescribing information.

Storage: Store in a refrigerator at 2-8°C/36-46°F. Protect from intense light. See package insert for additional information.

For more information, call
Mylan at 1-877-446-3679 (1-877-4-INFO-RX).

Manufactured for:
Mylan Specialty L.P.
Morgantown, WV 26505 U.S.A.

Manufactured by:
Woodstock Sterile Solutions, Inc.
Woodstock, IL 60098 U.S.A.

© 2021 Viatris Inc.

TOBI is a registered trademark of BGP Products Operations GmbH, a Viatris Company.

WS:345:56C:R1

PCR-700-13894